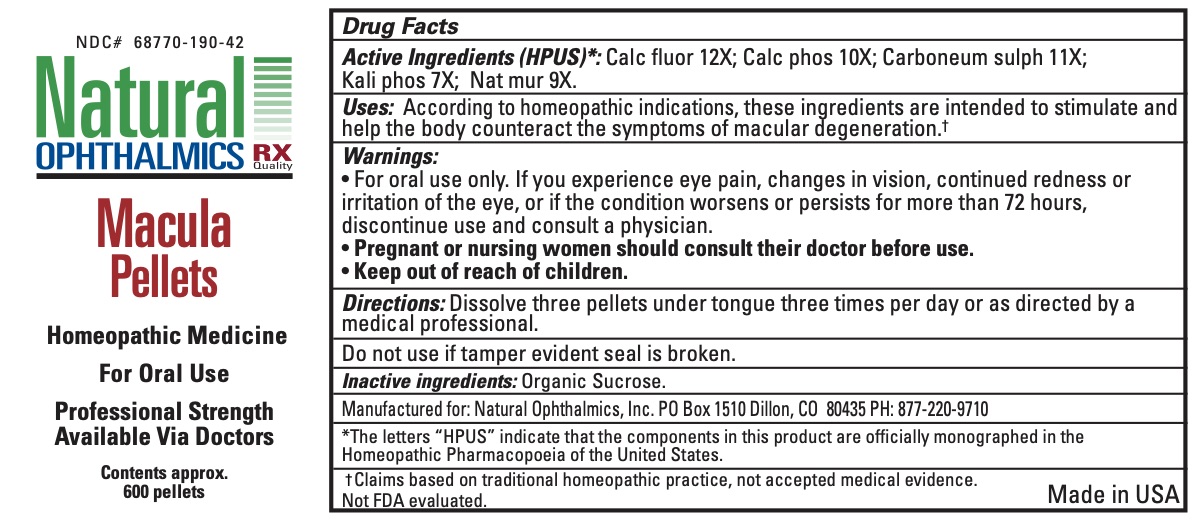 DRUG LABEL: Macula
NDC: 68770-190 | Form: PELLET
Manufacturer: Natural Ophthalmics, Inc
Category: homeopathic | Type: HUMAN OTC DRUG LABEL
Date: 20231231

ACTIVE INGREDIENTS: CALCIUM FLUORIDE 12 [hp_X]/1 1; CARBON DISULFIDE 11 [hp_X]/1 1; POTASSIUM PHOSPHATE, DIBASIC 7 [hp_X]/1 1; SODIUM CHLORIDE 9 [hp_X]/1 1; CALCIUM PHOSPHATE 10 [hp_X]/1 1
INACTIVE INGREDIENTS: SUCROSE

Macula Pellets

ACTIVE INGREDIENT

Calc fluor 12X; Calc phos 10X; Carboneum sulph 11X; Kali phos 7X; Nat mur 9X

Uses

Uses: According to homeopathic indications, these ingredients are intended to stimulate and help the body counteract the symptoms of macular degeneration.† .

Warnings:

• For oral use only. If you experience eye pain, changes in vision, continued redness or irritation of the eye, or if the condition worsens or persists for more than 72 hours, discontinue use and consult a physician.

PREGNANCY OR BREAST FEEDING

Pregnant or nursing women should consult their doctor before use.

Keep out of reach of children

INACTIVE INGREDIENT

organic sucrose

Directions:

Dissolve three pellets under tongue three times per day or as directed by a medical professional.

Do not use if tamper evident seal is broken.

*The letters “HPUS” indicate that the components in this product are officially monographed in the Homeopathic Pharmacopoeia of the United States.

† Claims based on traditional homeopathic practice, not accepted medical evidence.
Not FDA evaluated.

Manufactured for: Natural Ophthalmics, Inc. PO Box 1510 Dillon, CO 80435 PH: 877-220-9710